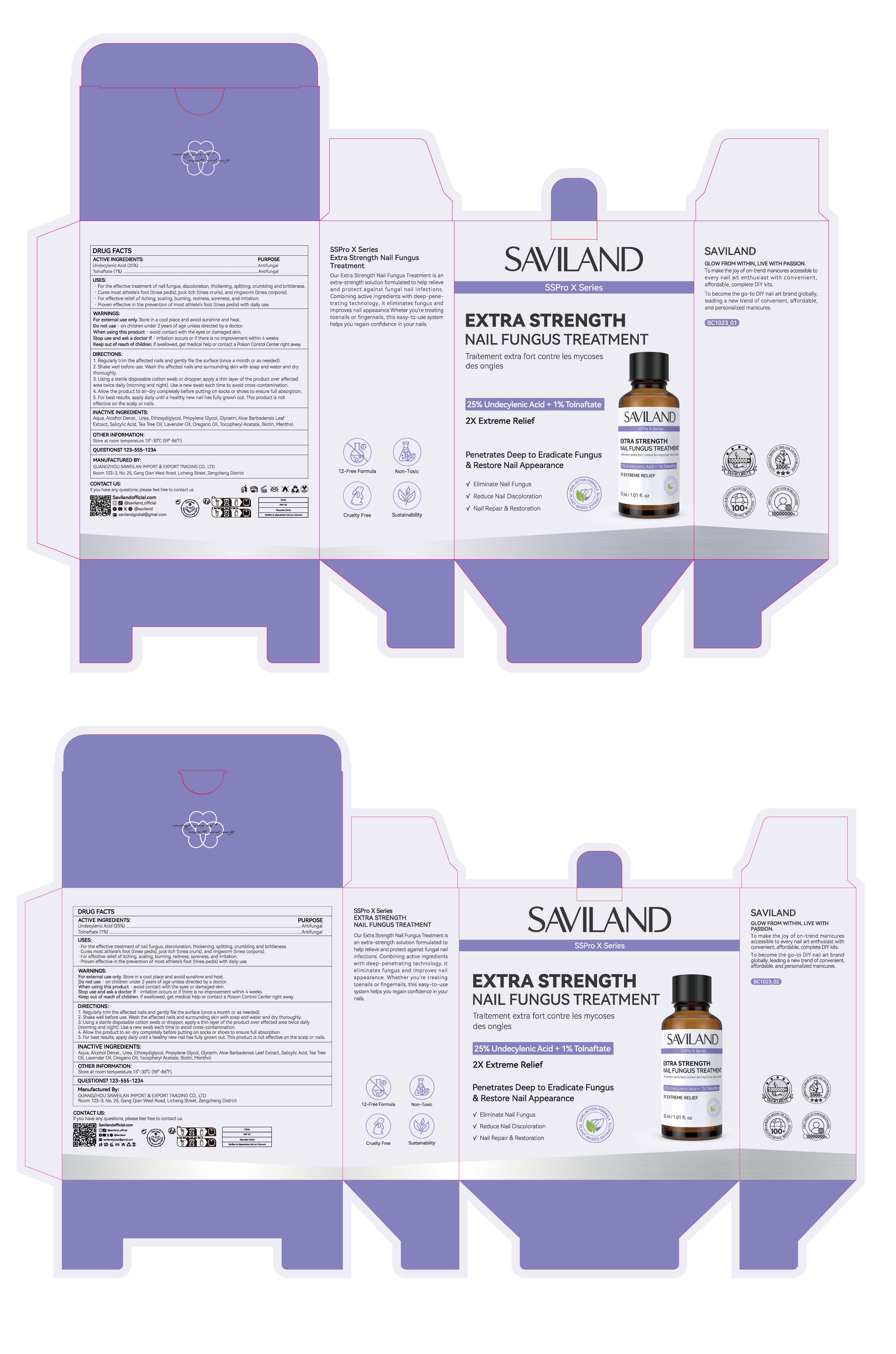 DRUG LABEL: Extra Strength Nail Fungus Treatment
NDC: 85966-001 | Form: LIQUID
Manufacturer: GUANGZHOU SAWEILAN IMPORT & EXPORT TRADING CO., LTD
Category: otc | Type: HUMAN OTC DRUG LABEL
Date: 20250902

ACTIVE INGREDIENTS: TOLNAFTATE 1 g/100 mL; UNDECYLENIC ACID 25 g/100 mL
INACTIVE INGREDIENTS: AQUA; BIOTIN; LAVENDER OIL; UREA; MENTHOL; ETHOXYDIGLYCOL; OREGANO LEAF OIL; SALICYLIC ACID; .ALPHA.-TOCOPHEROL ACETATE; TEA TREE OIL; PROPYLENE GLYCOL; GLYCERIN; ALCOHOL; ALOE BARBADENSIS LEAF POWDER

85966-001 Extra Strength Nail Fungus Treatment

ACTIVE INGREDIENT

UNDECYLENIC ACID 25%
TOLNAFTATE 1%

PURPOSE

Antifungal

INDICATIONS AND USAGE

For the effective treatment of nail fungus, discoloration, thickening, splitting, crumbling and brittleness
Cures most athlete's foot (tinea pedis), jock itch (tinea cruris), and ringworm (tinea corporis).
For effective relief of itching, scaling, burning, redness, soreness, and irritation.
Proven effective in the prevention of most athlete's foot (tinea pedis) with daily use.

WARNINGS

For external use only, Store in a cool place and avoid sunshine and heat.

Do not use on children under 2 years of age unless directed by a doctor

When using this product · avoid contact with the eyes or damaged skin.

Stop use and ask a doctor if . irritation occurs or if there is no improvement within 4 weeks.

Keep out of reach of children. lf swallowed, get medical help or contact a Poison Control Center right away.

DOSAGE AND ADMINISTRATION

1. Regularly trim the affected nails and gently file the surface (once a month or as needed).

2. Shake well before use. Wash the affected nails and surrounding skin with soap and water and dry thoroughly.

3. Using a sterile disposable cotton swab or dropper, apply a thin layer of the product over affectedarea twice daily (morning and night). Use a new swab each time to avoid cross-contamination.

4. Allow the product to air-dry completely before putting on socks or shoes to ensure full absorption.

5. For best results, apply daily until a healthy new nail has fully grown out. This product is noteffective on the scalp or nails.

INACTIVE INGREDIENT

UREA
ETHOXYDIGLYCOL
PROPYLENE GLYCOL
ALCOHOL DENAT.
TEA TREE OIL
OREGANO OIL
LAVENDER OIL
MENTHOL
ALOE BARBADENSIS LEAF EXTRACT
SALICYLIC ACID
BIOTIN/VITAMIN H
TOCOPHEROL ACETATE / VITAMIN E
AQUA
GLYCERIN